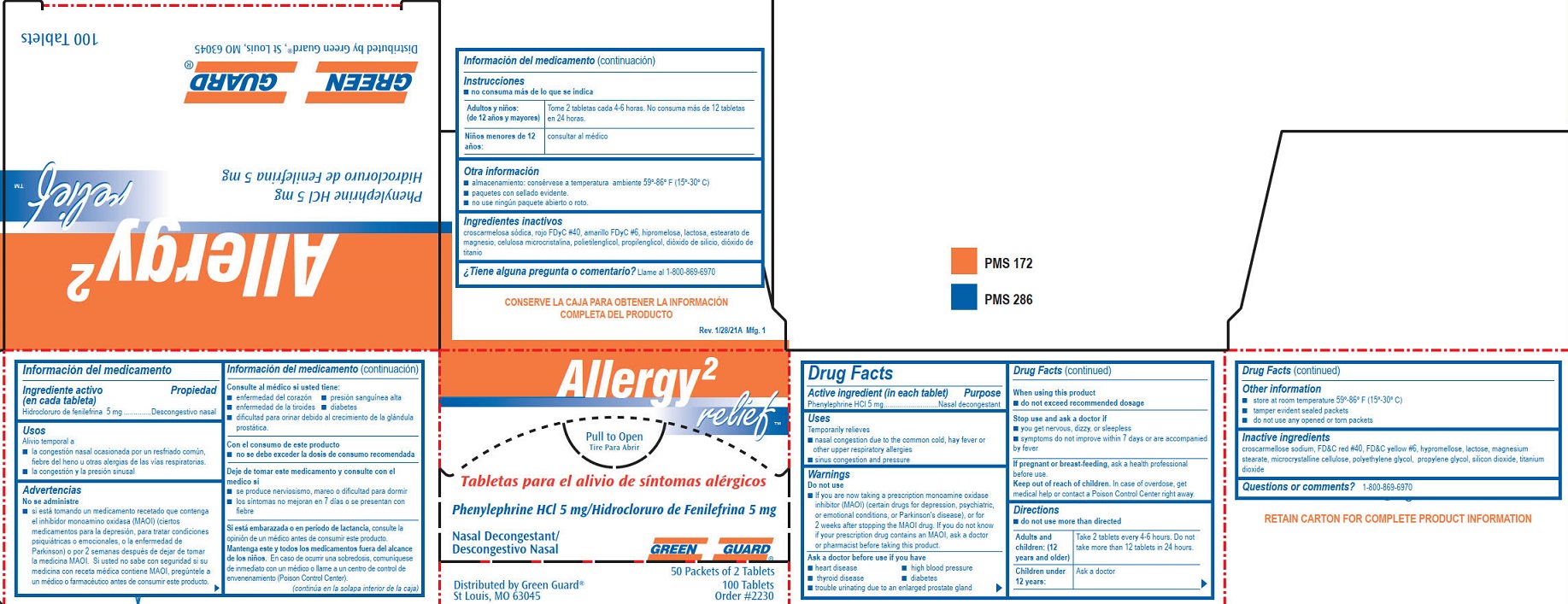 DRUG LABEL: Green Guard Allergy 2 Relief
NDC: 47682-017 | Form: TABLET, FILM COATED
Manufacturer: Unifirst First Aid Corporation
Category: otc | Type: HUMAN OTC DRUG LABEL
Date: 20250908

ACTIVE INGREDIENTS: PHENYLEPHRINE HYDROCHLORIDE 5 mg/1 1
INACTIVE INGREDIENTS: CELLULOSE, MICROCRYSTALLINE; CROSCARMELLOSE SODIUM; FD&C RED NO. 40; FD&C YELLOW NO. 6; HYPROMELLOSES; LACTOSE; MAGNESIUM STEARATE; POLYETHYLENE GLYCOL, UNSPECIFIED; SILICON DIOXIDE; TITANIUM DIOXIDE; PROPYLENE GLYCOL

205R Phenylephrine Green Guard Allergy 2 Relief

Drug Facts

Active ingredient (in each tablet)

Phenylephrine HCl 5mg

Purpose

Nasal decongestant

Uses

Temporarily relieves

■ nasal congestion due to the common cold, hay fever or other upper respiratory allergies

■ sinus congestion and pressure

Warnings

Do not use

- If you are now taking a prescription monoamine oxidase inhibitor (MAOI) (certain drugs for depression, psychiatric, or emotional conditions, or Parkinson's disease), or for 2 weeks after stopping the MAOI drug. If you do not know if your prescription drug contains an MAOI, ask a doctor or pharmacist before taking this product.

Ask a doctor before use if you have

- heart disease
- high blood pressure
- thyroid disease
- diabetes
- trouble urinating due to an enlarged prostate gland

When using this product

■ do not exceed recommended dosage

Stop use and ask a doctor if

■ you get nervous, dizzy, or sleepless

■ symptoms do not improve within 7 days or are accompanied by fever

PREGNANCY OR BREAST FEEDING

If pregnant or breast-feeding, ask a health professional before use.

Keep out of reach of children. In case of overdose, get medical help or contact a Poison Control Center right away.

Directions

- do not use more than directed

Adults and children: (12 years and older) Take 2 tablets every 4 - 6 hours. Do not take more than 12 tablets in 24 hours.

Children under 12 years: Ask a doctor

Other information

- store at room temperature 59º-86º F (15º-30º C).
- tamper evident sealed packets.
- do not use any opened or torn packets

Inactive ingredients

croscarmellose sodium, FD&C red #40, FD&C yellow #6, hypromellose, lactose, magnesium stearate, microcrystalline cellulose, polyethylene glycol, propylene glycol, silicon dioxide, titanium dioxide

Questions or comments? 1-800-869-6970

Green Guard Allergy 2 Relief Label

Allergy 2 relief™
Pull To Open

Tire Para Abrir

Tabletas para el alivio de
sintomas alergicos
Phenylephrine HCl 5mg/ Hidrocloruro de Fenilefrina 5mg
Nasal Decongestant/ Descongestivo Nasal

Green Guard®
50 Packets of 2 Tablets
100 Tablets
Order #2230
Distributed by Green Guard®, St Louis, MO 63045